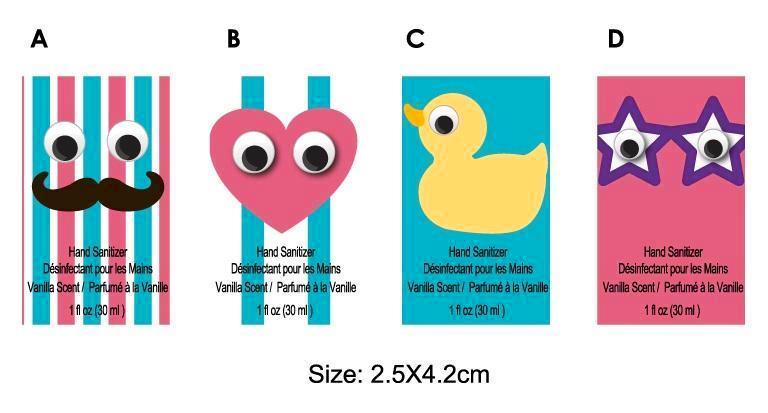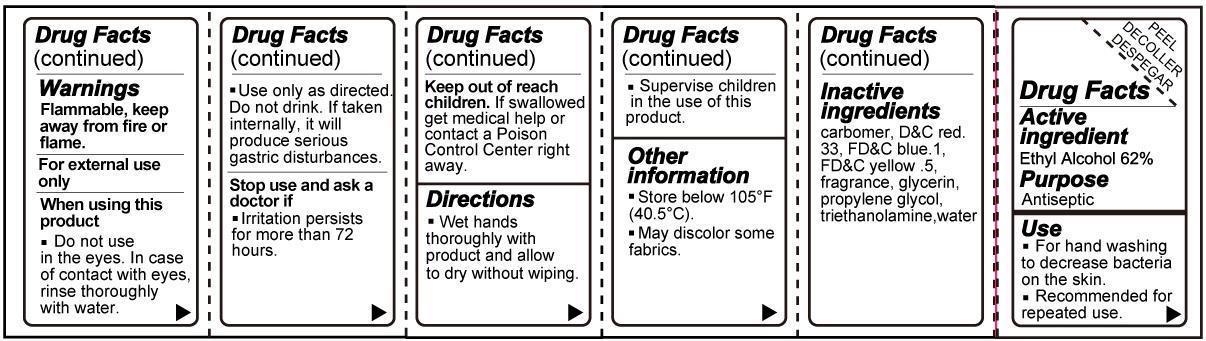 DRUG LABEL: Hand Sanitizer Vanilla Scent
NDC: 60675-004 | Form: GEL
Manufacturer: Michaels Stores Procurement Company
Category: otc | Type: HUMAN OTC DRUG LABEL
Date: 20140924

ACTIVE INGREDIENTS: ALCOHOL 62 mL/100 mL
INACTIVE INGREDIENTS: D&C RED NO. 33; FD&C BLUE NO. 1; FD&C YELLOW NO. 5; GLYCERIN; PROPYLENE GLYCOL; TROLAMINE; WATER

Hand Sanitizer Vanilla Scent

Active Ingredient

Ethyl Alcohol 62%

Purpose

Antiseptic

Use

- For hand washing to decrease bacteria on the skin
- Recommended for repeated use.

Warnings

- Flammable, keep away from fire or flame.
- For external use only.
- Do not use in the eyes. In case of contact with eyes, rinse thoroughly with water.
- Use only as directed. Do not drink. If taken internally, it will produce serious gastric disturbances.
- Stop use and ask a doctor if irritation persists for more than 72 hours.

- Keep out of reach of children. If swallowed, get medical help or contact a Poison Control Center right away.

Directions

- Wet hands thoroughly with product and allow to dry without wiping.
- Supervise children in the use of this product.

Other information

- Store below 105 degrees F (40.5 degrees C).
- May discolor some fabrics.

Inactive Ingredients

- carbomer, DandC red n 33, FDandC blue n 1, FDandC yellow n 5, fragrance, glycerin, propylene glycol, triethanolamine, water